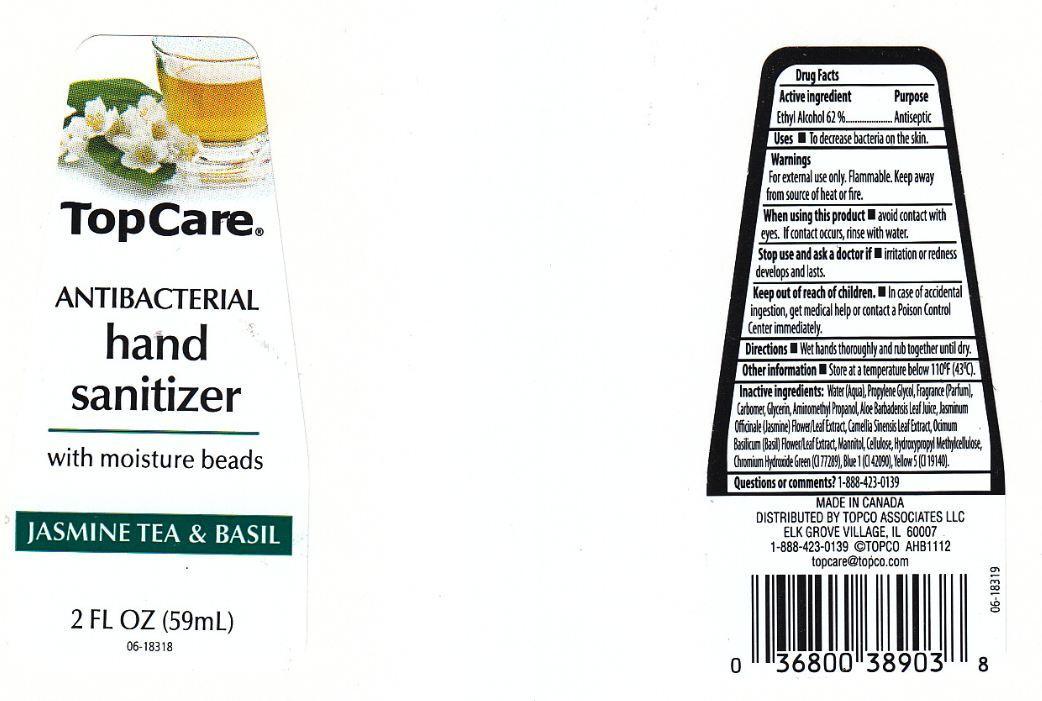 DRUG LABEL: TOPCARE
NDC: 36800-266 | Form: LIQUID
Manufacturer: TOPCO ASSOCIATES LLC
Category: otc | Type: HUMAN OTC DRUG LABEL
Date: 20130321

ACTIVE INGREDIENTS: ALCOHOL 620 mg/1 mL
INACTIVE INGREDIENTS: WATER; PROPYLENE GLYCOL; CARBOMER 934; GLYCERIN; AMINOMETHYLPROPANOL; ALOE VERA LEAF; JASMINUM OFFICINALE FLOWER; GREEN TEA LEAF; OCIMUM BASILICUM FLOWERING TOP; MANNITOL; POWDERED CELLULOSE; HYPROMELLOSES; CHROMIUM HYDROXIDE GREEN; FD&C BLUE NO. 1; FD&C YELLOW NO. 5

DRUG FACTS

ACTIVE INGREDIENT

ETHYL ALCOHOL 62%

PURPOSE

ANTISEPTIC

USES

TO DECREASE BACTERIA ON THE SKIN.

WARNINGS

FOR XTERNAL USE ONLY. FLAMMABLE. KEEP AWAY FROM SOURCE OF HEAT OR FIRE.

WHEN USING THIS PRODUCT

AVOID CONTACT WITH EYES. IF CONTACT OCCURS, RINSE WITH WATER.

STOP USE AND ASK A DOCTOR IF

IRRITATION OR REDNESS DEVELOPS AND LASTS.

KEEP OUT OF REACH OF CHILDREN.

IN CASE OF ACCIDENTAL INGESTION, GET MEDICAL HELP OR CONTACT A POISON CONTROL CENTER IMMEDIATELY.

DIRECTIONS

WET HANDS THOROUGHLY AND RUB TOGETHER UNTIL DRY.

OTHER INFORMATION

STORE AT A TEMPERATURE BELOW 110F (43C).

INACTIVE INGREDIENTS:

WATER (AQUA), PROPYLENE GLYCOL, FRAGRANCE (PARFUM), CARBOMER, GLYCERIN, AMINOMETHYL PROPANOL, ALOE BARBADENSIS LEAF JUICE, JASMINUM OFFICINALE (JASMINE) FLOWER/LEAF EXTRACT, CAMELLIA SINENSIS LEAF EXTRACT, OCIMUM BASILICUM (BASIL) FLOWER/LEAF EXTRACT, MANNITOL, CELLULOSE, HYDROXYPROPYL METHYLCELLULOSE, CHROMIUM HYDROXIDE GREEN (CI 77289), BLUE 1 (CI 42090), YELLOW 5 (CI 19140).

QUESTIONS OR COMMENTS?

1-888-423-0139